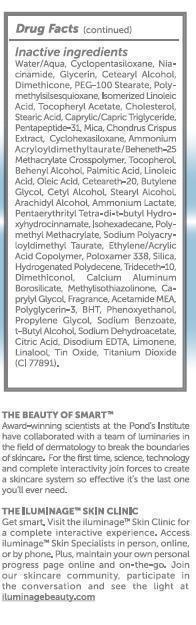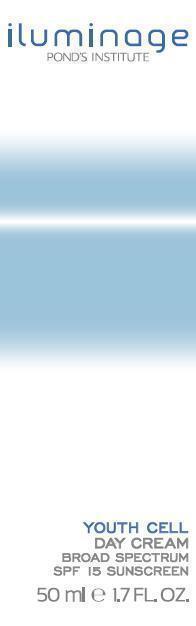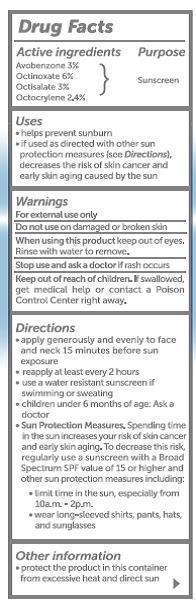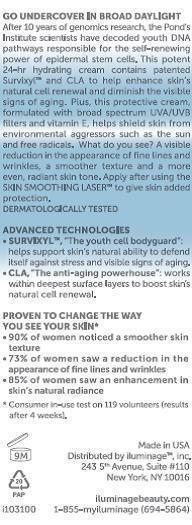 DRUG LABEL: Youth Cell Day Cream Broad Spectrum SPF-15 Sunscreen (50 ml)
NDC: 69047-001 | Form: CREAM
Manufacturer: Iluminage Beauty, Inc.
Category: otc | Type: HUMAN OTC DRUG LABEL
Date: 20140620

ACTIVE INGREDIENTS: OCTINOXATE 5.994 mg/100 mL; OCTISALATE 3.000 mg/100 mL; OCTOCRYLENE 2.400 mg/100 mL; AVOBENZONE 3.000 mg/100 mL
INACTIVE INGREDIENTS: ACETAMIDE; AMMONIUM ACRYLOYLDIMETHYLTAURATE/BEHENETH-25 METHACRYLATE CROSSPOLYMER (52000 MPA.S); AMMONIUM LACTATE; ARACHIDYL ALCOHOL; DOCOSANOL; BUTYLATED HYDROXYTOLUENE; BUTYLENE GLYCOL; CALCIUM ALUMINUM BOROSILICATE; MEDIUM-CHAIN TRIGLYCERIDES; CAPRYLYL GLYCOL; POLYOXYL 20 CETOSTEARYL ETHER; CETOSTEARYL ALCOHOL; CETYL ALCOHOL; CHLORPHENESIN; CHOLESTEROL; CHONDRUS CRISPUS; CITRIC ACID MONOHYDRATE; CYCLOMETHICONE 6; CYCLOMETHICONE 5; CYCLOMETHICONE 4; DIMETHICONE; DIMETHICONOL (2000 CST); EDETATE DISODIUM; GLYCERIN; HYDROGENATED POLYDECENE (550 MW); ISOHEXADECANE; LINOLEIC ACID; METHYLISOTHIAZOLINONE; MICA; NIACINAMIDE; OLEIC ACID; PALMITIC ACID; PEG-100 STEARATE; PENTAERYTHRITOL TETRAKIS(3-(3,5-DI-TERT-BUTYL-4-HYDROXYPHENYL)PROPIONATE); PHENOXYETHANOL; POLOXAMER 338; POLY(METHYL METHACRYLATE; 450000 MW); POLYMETHYLSILSESQUIOXANE (4.5 MICRONS); PROPYLENE GLYCOL; SILICON DIOXIDE; SODIUM BENZOATE; SODIUM DEHYDROACETATE; STEARIC ACID; STEARYL ALCOHOL; TERT-BUTYL ALCOHOL; STANNIC OXIDE; TITANIUM DIOXIDE; .ALPHA.-TOCOPHEROL ACETATE; TRIDECETH-10; WATER

PACKAGE LABEL

Iluminage

POND'S INSTITUTE

YOUTH CELL

DAY CREAM

BROAD SPECTRUM

SPF 15 SUNSCREEN

50 ml e 1 .7 FL. OZ

PACKAGE LABEL

GO UNDERCOVER IN BROAD DAYLIGHT

After 10 years of genomics research, the Pond’s

Institute scientists have decoded youth DNA

Pathways responsible for the self-renewing

Power of epidermal stem cells. This potent

24-hr hydrating cream contains patented

Survixyl ™ and CLA to help enhance skin’s

natural cell renewal and diminish the visible

signs of aging. Plus, this protective cream

formulated with board spectrum UVA/UVB

filters and vitamin E, helps shield skin from

environmental aggressors such as the sun

and free radicals, What do you see? A visible

reduction in the appearance of fine lines and

wrinkles, a smoother texture and a more

even, radiant skin tone. Apply after using the

SKIN SMOOTHING LASER™ to give skin added

protection.

DERMATOLOGIST TESTED

ADVANCE TECHNOLOGIES

-SURVIXYL™, “The youth cell bodyguard:

Helps support skin’s natural ability to defend

itself against stress and visible signs of aging.

-CLA, “The anti-aging power house”: works

within deepest surface layers to boost skin’s

natural cell renewal.

PROVEN TO CHANGE THE WAY

YOU SEE YOUR SKIN*

-90% of women noticed a smoother skin

Texture.

-73% of women saw a reduction in the

appearance of fine lines and wrinkles

-85% of women saw an enhancement in

skin’s natural radiance

*Consumer in-use test on 119 volunteers (results after 4 weeks).

Made in USA

Distributed by Iluminage™, inc.

243 5th Avenue, Suite #110

New York, NY 10016

Iluminagebeauty.com

I103100 1-855-myiluminage (694-5864)

Drug Facts

Active ingredients

Avobenzone 3%

Octinoxate 6%

Octisalate 3%

Octocrylene 2.4%

Purpose

Sunscreen

Uses

-helps prevent sunburn

If used as directed with other sun

protection measures (See Directions),

decreases the risk of skin cancer and

early skin aging cause by the sun.

Warnings

For external use only

Do not use on damaged or broken skin

When using this product keep out of eyes.

Rinse with water to remove.

Stop use and ask a doctor if rash occurs

Keep out of reach of children. If swallowed,

get medical help or contact a Poison

Control Center right away.

Directions

-apply generously and evenly to face

and neck 15 minutes before sun

exposure.

-reapply at least every 2 hours

-use a water resistant sunscreen if

swimming or sweating.

-children under 6 months of age. Ask a

doctor

-Sun Protection Measures, Spending time

in the sun increases your risk of skin cancer

and early skin aging. To decrease this risk,

regularly use a sunscreen with a Board

Spectrum SPF value of 15 or higher and

other sun protection measures including:

-limit time in the sun, especially from

10 a.m. – 2 p.m.

-wear long-sleeved shirts, pants, hats,

and sunglasses.

Other information

-protect the product in this container

from excessive heat and direct sun

PACKAGE LABEL

Drug Facts (continued)

Inactive ingredients

Water/Aqua, Cyclopentasiloxane, Nia-

cinamide, Glycerin, Cetearyl Alcohol,

Dimethicone, PEG-100 Stearate, Poly-

Methylsilsesquixane, Isomerized Linoleic

Acid, Tocopheryl Acetate, Cholesterol,

Stearic Acid, Caprylic/Capric Triglyceride,

Pentapeptide-31, Ammonium

Acryloydimethyltaurate/Beheneth-25

Methylacrylate Crosspolymer, Tocopherol,

Behenyl Alcoho, Palmitic Acid, Linoleic

Acid, Oleic Acid, Ceteareth-20, Butylene

Glycol, Cetyl Alcohol, Stearyl Alcohol,

Arachidyl Alcohol, Ammonium Lactate,

Pentaerythiryl Tetra-di-t-butyl Hydro-

Xyhydrocinnamate, Isohexadecane, Poly-

Methyl Methacrylate, Sodium Polyacry-

Loyldimethyl Taurate, Ethylene/Arcylic

Acid Copolymer, Poloxamer 338, Silica,

Hydrogenated Polydecene, Trideceth-10,

Dimethiconol, Calcium Aluminum

Borosilicate, Methylisothiszolinone, Cap-

prylyl Glycol, Fragrance, Acetamide MEA,

Polyglycerin-3, BHT, Phenoxyethanol,

Propylene Glycol, Sodium Benzoate,

Citric Acid, Disodium EDTA, Limonene,

Linalool, tin Oxide. Titanium Dioxide

(CI 77891).

THE BEAUTY OF SMART™

Award-winning scientists at the Pond’s Institute

have collaborated with a team of luminaries in

the field of dermatology to break the boundaries

of skincare. For the first time, science, technology

and complete interactivity join forces to create

a skincare system so effective it’s the last one

you’ll ever need.

THE ILUMINAGE ™ SKIN CLINIC

Get smart. Visit the Iluminage ™ Skin Clinic for

A complete interactive experience. Access

Iluminage ™ Skin Specialists in person, online,

Or by phone. Plus, maintain your own personal

Progress page online and on-the-go. Join

Our skincare community, participate in

the conversation and see the light at

iluminagebeauty.com

ACTIVE INGREDIENT

Avobenzone 3%

Octinoxate 6%

Octisalate 3%

Octocrylene 2.4%

PURPOSE

Sunscreen

Warnings

For external use only

Do not use on damaged or broken skin

When using this product keep out of eyes.

Rinse with water to remove.

Stop use and ask a doctor if rash occurs

Keep out of reach of children. If swallowed,

get medical help or contact a Poison

Control Center right away.

Directions

-apply generously and evenly to face

and neck 15 minutes before sun

exposure.

-reapply at least every 2 hours

-use a water resistant sunscreen if

swimming or sweating.

OTHER SAFETY INFORMATION

-children under 6 months of age. Ask a

doctor

-Sun Protection Measures, Spending time

in the sun increases your risk of skin cancer

and early skin aging. To decrease this risk,

regularly use a sunscreen with a Board

Spectrum SPF value of 15 or higher and

other sun protection measures including:

-limit time in the sun, especially from

10 a.m. – 2 p.m.

-wear long-sleeved shirts, pants, hats,

and sunglasses.

Inactive ingredients

Water/Aqua, Cyclopentasiloxane, Nia-

cinamide, Glycerin, Cetearyl Alcohol,

Dimethicone, PEG-100 Stearate, Poly-

Methylsilsesquixane, Isomerized Linoleic

Acid, Tocopheryl Acetate, Cholesterol,

Stearic Acid, Caprylic/Capric Triglyceride,

Pentapeptide-31, Ammonium

Acryloydimethyltaurate/Beheneth-25

Methylacrylate Crosspolymer, Tocopherol,

Behenyl Alcoho, Palmitic Acid, Linoleic

Acid, Oleic Acid, Ceteareth-20, Butylene

Glycol, Cetyl Alcohol, Stearyl Alcohol,

Arachidyl Alcohol, Ammonium Lactate,

Pentaerythiryl Tetra-di-t-butyl Hydro-

Xyhydrocinnamate, Isohexadecane, Poly-

Methyl Methacrylate, Sodium Polyacry-

Loyldimethyl Taurate, Ethylene/Arcylic

Acid Copolymer, Poloxamer 338, Silica,

Hydrogenated Polydecene, Trideceth-10,

Dimethiconol, Calcium Aluminum

Borosilicate, Methylisothiszolinone, Cap-

prylyl Glycol, Fragrance, Acetamide MEA,

Polyglycerin-3, BHT, Phenoxyethanol,

Propylene Glycol, Sodium Benzoate,

Citric Acid, Disodium EDTA, Limonene,

Linalool, tin Oxide. Titanium Dioxide

(CI 77891).